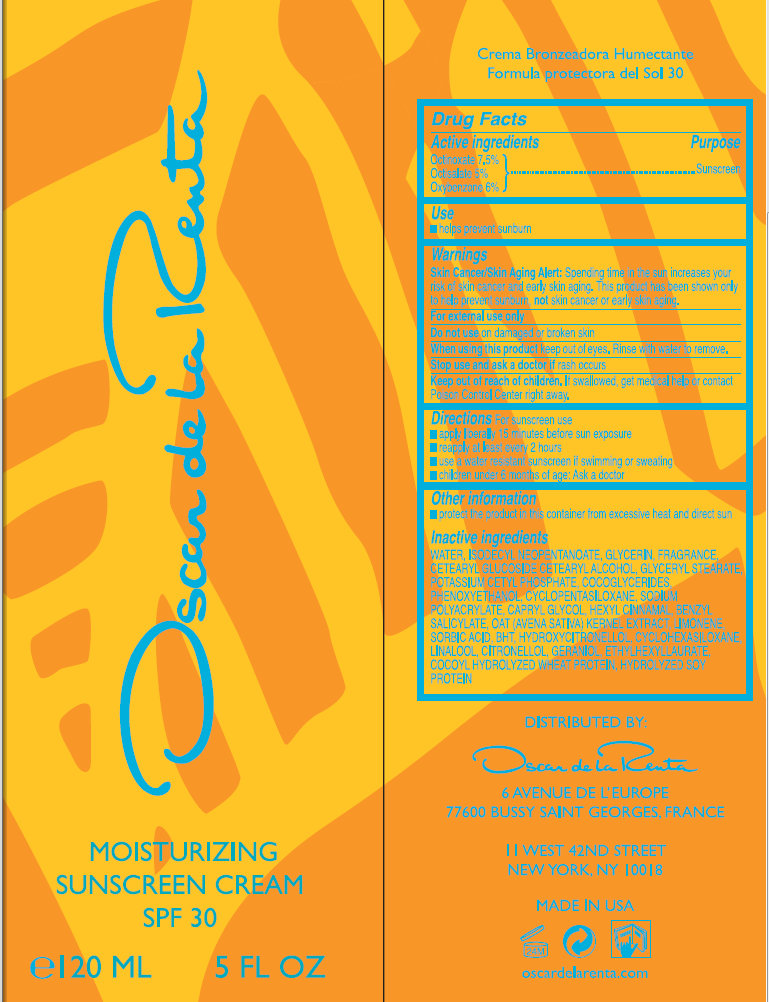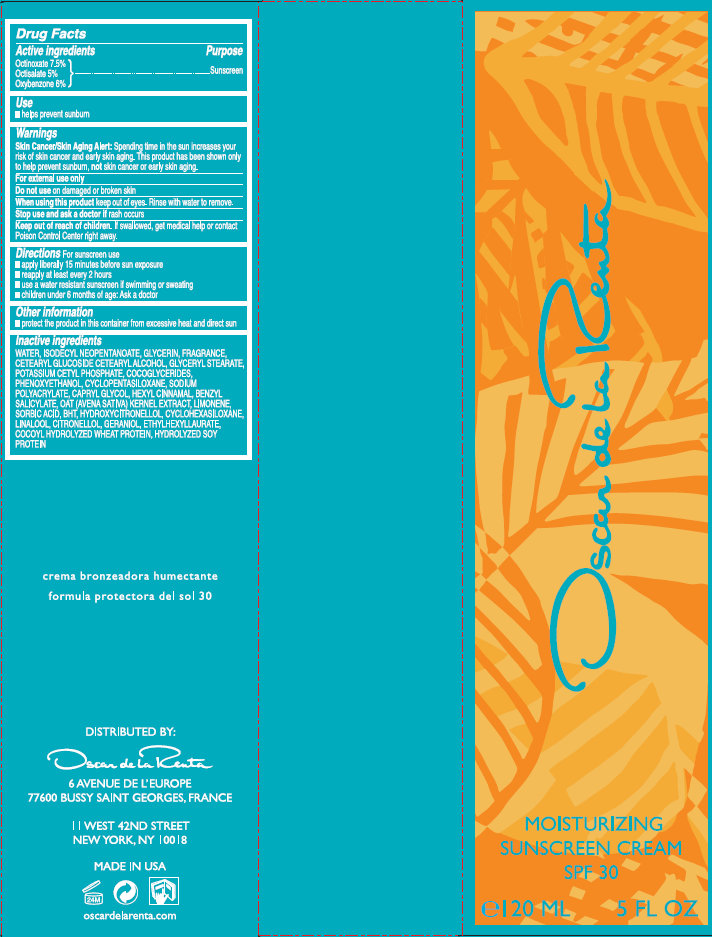 DRUG LABEL: Oscar de la Renta Moisturizing Sunscreen SPF 30
NDC: 45124-001 | Form: CREAM
Manufacturer: Oscar de la Renta LLC
Category: otc | Type: HUMAN OTC DRUG LABEL
Date: 20120411

ACTIVE INGREDIENTS: OCTINOXATE 7.5 mL/100 mL; OCTISALATE 5 mL/100 mL; OXYBENZONE 6 mL/100 mL
INACTIVE INGREDIENTS: WATER; ISODECYL NEOPENTANOATE; GLYCERIN; CETEARYL GLUCOSIDE; CETOSTEARYL ALCOHOL; GLYCERYL MONOSTEARATE; POTASSIUM CETYL PHOSPHATE; COCO-GLYCERIDES; PHENOXYETHANOL; CYCLOMETHICONE 5; SODIUM POLYACRYLATE (8000 MW); CAPRYLYL GLYCOL; .ALPHA.-HEXYLCINNAMALDEHYDE; BENZYL SALICYLATE; OAT; SORBIC ACID; BUTYLATED HYDROXYTOLUENE; HYDROXYCITRONELLOL; CYCLOMETHICONE 6; LINALOOL, (+/-)-; GERANIOL; ETHYLHEXYL LAURATE; SOY PROTEIN

Oscar de la Renta Moisturizing Sunscreen Cream SPF 30

Active ingredients

Octinoxate 7.5%
Octisalate 5%
Oxybenzone 6%

Use

- helps prevent sunburn

Warnings

Skin Cancer/Skin Aging Alert: Spending time in the sun increases your risk of skin cancer and early skin aging. This product has been shown only to help prevent sunburn, not skin cancer or early skin aging.

For external use only

Do not use

on damaged or broken skin

When using this product

keep out of eyes. Rinse with water to remove.

Stop use and ask a doctor if

rash occurs

Keep out of reach of children

If swallowed, get medical help or contact Poison Control Center right away.

Directions

For sunscreen use

- apply liberally 15 minutes before sun exposure
- reapply at least every 2 hours
- use a water resistant sunscreen if swimming or sweating
- children 6 months of age: Ask a doctor

Other information

- protect the product in this container from excessive heat and direct sun

Inactive ingredients

WATER, ISODECYL NEOPENTANOATE, GLYCERIN, FRAGRANCE, CETEARYL GLUCOSIDE, CETEARYL ALCOHOL, GLYCERYL STEARATE, POTASSIUM CETYL PHOSPHATE, COCOGLYCERIDES, PHENOXYETHANOL, CYCLOPENTASILOXANE, SODIUM POLYACRYLATE, CAPRYLYL GLYCOL, HEXYL CINNAMAL, BENZYL SALICYLATE, OAT (AVENA SATIVA) KERNEL EXTRACT, LIMONENE, SORBIC ACID, BHT, HYDROXYCITRONELLOL, CYCLOHEXASILOXANE, LINALOOL, CITRONELLOL, GERANIOL, ETHYLHEXYLLAURATE, COCOYL HYDROLYZED WHEAT PROTEIN, HYDROLYZED SOY PROTEIN

Purpose

Sunscreen

PACKAGE LABEL

Oscar de La Renta MOISTURIZING SUNSCREEN CREAM SPF 30 e120 ML 5 FL OZ
DISTRIBUTED BY: Oscar de La Renta 6 AVENUE DEL'EUROPE 77600 BUSSY SAINT GEORGES, FRANCE
II WEST 42ND STREET NEW YORK, NY 10018 MADE IN USE oscardelarenta.com